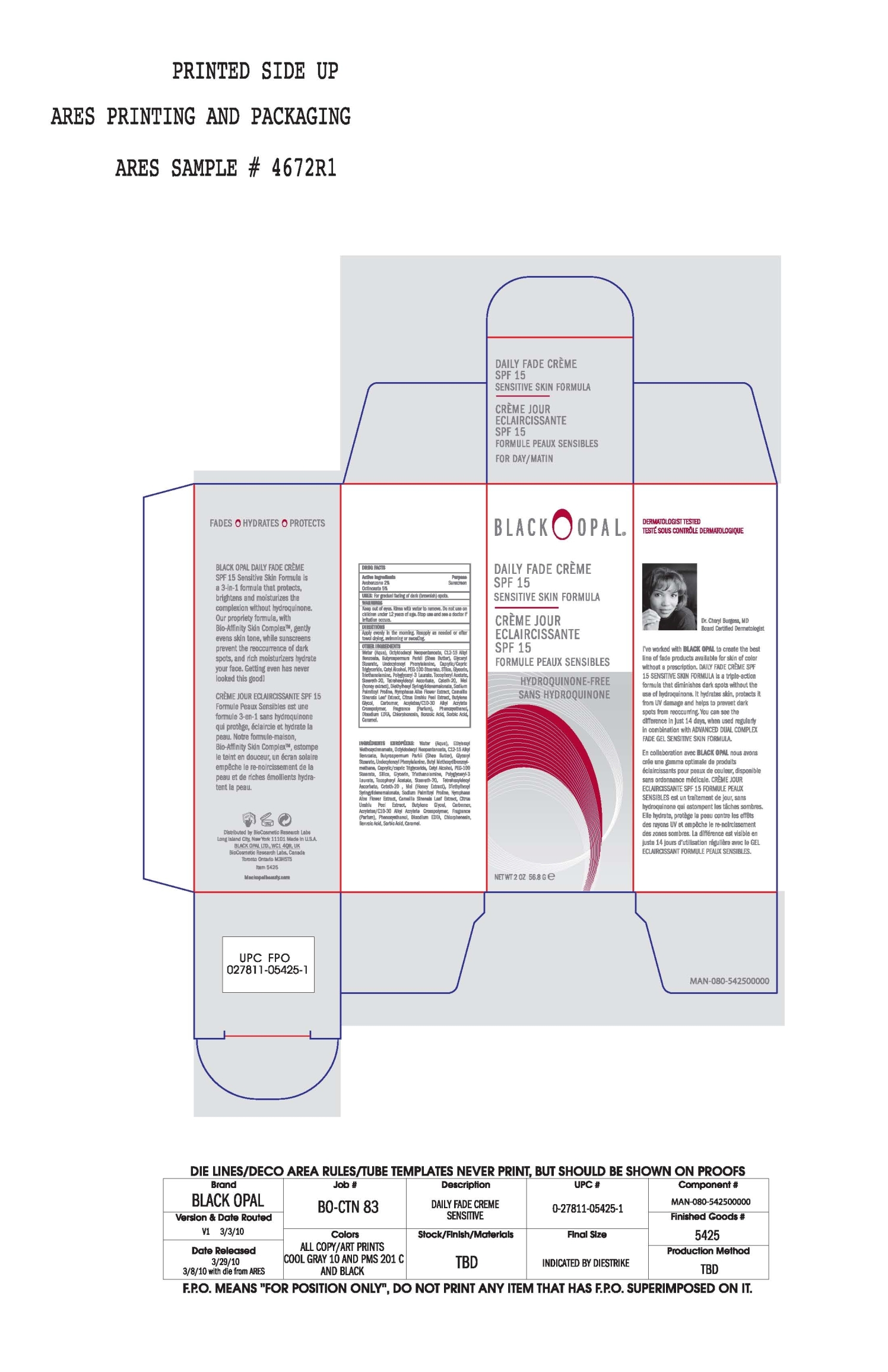 DRUG LABEL: Daily Fade 
NDC: 59735-306 | Form: CREAM
Manufacturer: Biocosetic Research Labs
Category: otc | Type: HUMAN OTC DRUG LABEL
Date: 20060306

ACTIVE INGREDIENTS: Avobenzone 2 g/100 g; Octinoxate 5 g/100 g

Daily Fade Creme SPF15

Active Ingredients

Avobenzone 2%

Octinoxate 5%

Purpose

Sunscreen

Uses

For gradual fading of dark {brownish} spots.

Warnings

Keep out of eyes. Rinse with water to remove.

Do not use on children under 12 years of age.

Stop use and see a doctor if irritation occurs.

Directions

Apply evenly in the morning. Reapply as needed or after towel drying, swimming or sweating.

INACTIVE INGREDIENT

Other Ingredients

Water (Aqua), Octyldodecyl Neopentanoate, C12-15 Alkyl Benzoate, BUtyrosermum Parkii (Shea Butter), Glyceryl Stearate, Undecylenoyl phenylalanine, Caprylic/Capric Triglyceride, Cetyl Alcohol, PEG-100 Stearate, Silica, Glycerin, Triethanolamine, Polyglyceryl-3 Laurate, Tocopheryl Acetate,Steareth-20, Tetrahexyldecyl Ascorbate, Ceteth-20, Mel {honey extract}, Diethylhexyl Syringylidenemalonate, Sodium Palmitoyl Proline, Nymphaea Alba Flower Extract,, Camellia Sinensis Leaf Extract, Citrus Unshiu Peel Extract, Butylene Glycol, Carbomer, Acrylates/C10-30 Alkyl Acrylate Crosspolymer, Fragrance (Parfum), Phenoxyethanol, Disodium EDTA, Chlorphenesin, Benzoic Acid, Sorbic Acid, Caramel.